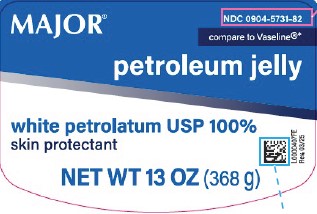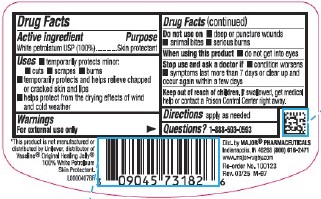 DRUG LABEL: Petroleum Skin Protectant
NDC: 0904-5731 | Form: JELLY
Manufacturer: Major Pharmaceuticals
Category: otc | Type: HUMAN OTC DRUG LABEL
Date: 20260204

ACTIVE INGREDIENTS: PETROLATUM 1 g/1 g

Major 069.001/069AA
Petroleum Jelly

Active ingredient

White Petrolatum USP (100%)

Purpose

Skin protectant

Uses

- temporarily protects minor: cuts- scrapes- burns
- temporarily protects and helps relieve chapped or cracked skin and lips
- helps protects from the drying effects of wind and cold weather

Warnings

For external use only

Do not use on

- deep or puncture wounds
- animal bites
- serious burns

When using this product

- do not get into eyes

Stop use and ask a doctor if

- condition worsens
- symptoms last more than 7 days or clear up and occur again within a few days

Keep out of reach of children.

If swallowed, get medical help or contact a Poison Control Center right away.

Directions

apply as needed

Inactive ingredient

None

Questions?

1-888-593-0593

Dislcaimer

*This product is not manufactured or distributed by Unilever, distributor of Vaseline® Original Healing JellySkin Protectant.

ADVERSE REACTION

Dist. by MAJOR®PHARMACEUTICALS

Indianapolis, IN 46268 (800) 616-2471

www.major-rugby.com

Re-order No. 100123

Rev. 03/25 M-97

principal display panel

NDC 0904-5731-82

MAJOR®

Compare to Vaseline®*

Petroleum Jelly

White Petrolatum USP 100%

Skin Protectant

NET WT 13 OZ (368 g)

Rev. 03/25